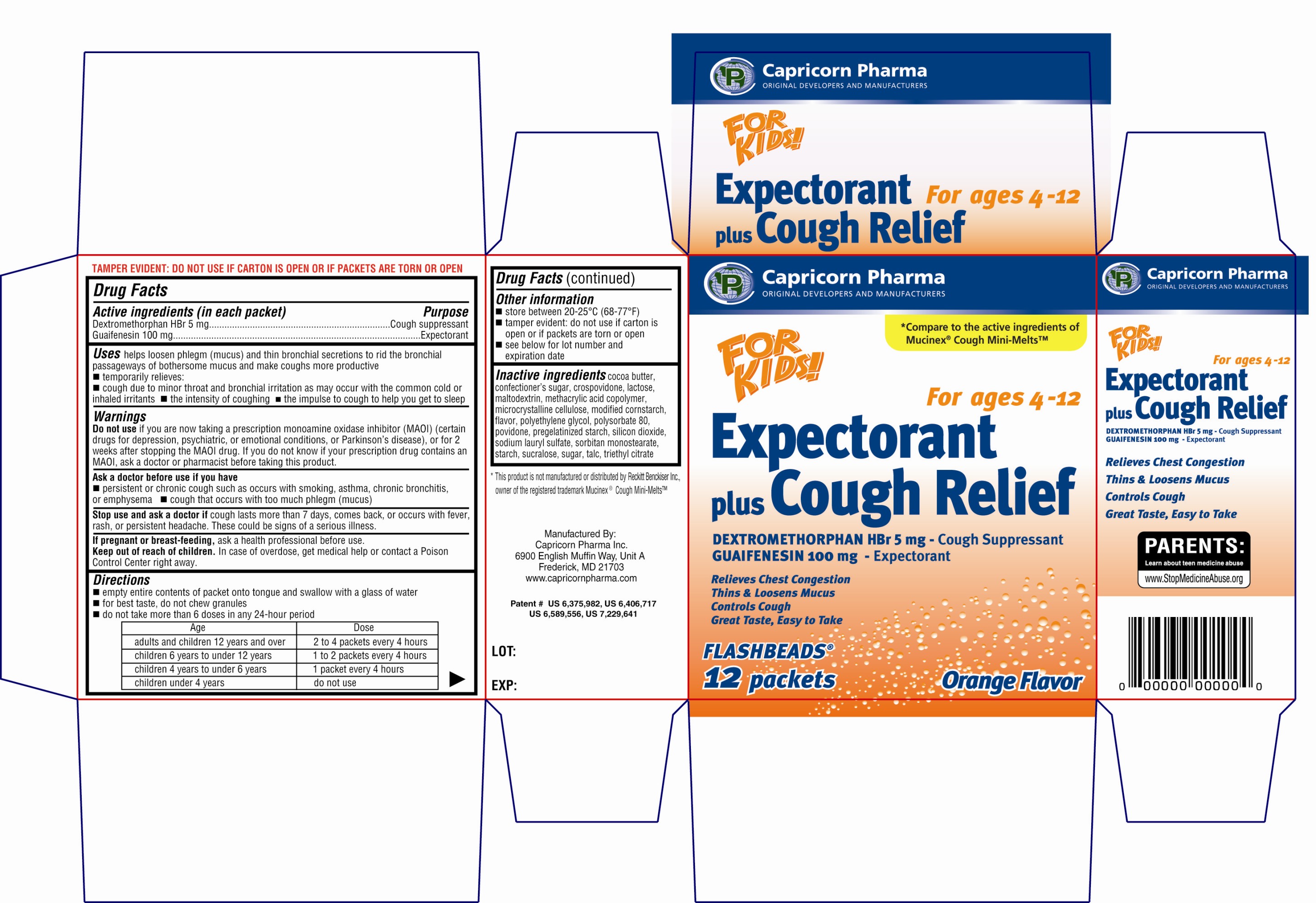 DRUG LABEL: Expectorant plus Cough Relief
NDC: 66007-204 | Form: GRANULE
Manufacturer: Capricorn Pharma Inc.
Category: otc | Type: HUMAN OTC DRUG LABEL
Date: 20100806

ACTIVE INGREDIENTS: DEXTROMETHORPHAN HYDROBROMIDE 5 mg/1 1; GUAIFENESIN 100 mg/1 1

Drug Facts

Active Ingredients (in each packet)

Dextromethorphan HBr 5mg

Guaifenesin 100mg

Purpose

Cough Suppressant

Expectorant

Uses

helps loosen phlegm (mucus) and thin bronchial secretions to rid the bronchial passageways of bothersome mucus and make coughs more productive
■ temporarily relieves:
■ cough due to minor throat and bronchial irritation as may occur with the common cold or inhaled irritants
■ the intensity of coughing
■ the impulse to cough to help you get to sleep

Warnings

Do not use if you are now taking a prescription monoamine oxidase inhibitor (MAOI) (certain drugs for depression, psychiatric, or emotional conditions, or Parkinson’s disease), or for 2 weeks after stopping the MAOI drug. If you do not know if your prescription drug contains an MAOI, ask a doctor or pharmacist before taking this product.

Ask a doctor before use if you have

■ persistent or chronic cough such as occurs with smoking, asthma, chronic bronchitis, or emphysema
■ cough that occurs with too much phlegm (mucus)

Stop use and ask a doctor if cough lasts more than 7 days, comes back, or occurs with fever, rash, or persistent headache. These could be signs of a serious illness.

PREGNANCY OR BREAST FEEDING

If pregnant or breast-feeding, ask a health professional before use.

Keep out of reach of children. In case of overdose, get medical help or contact a Poison Control Center right away.

Directions

■ empty entire contents of packet onto tongue and swallow with a glass of water
■ for best taste, do not chew granules
■ do not take more than 6 doses in any 24-hour period

Age | Dose
adults and children 12 years and over | 2 to 4 packets every 4 hours
children 6 years to under 12 years | 1 to 2 packets every 4 hours
children 4 years to under 6 years | 1 packet every 4 hours
children under 4 years | do not use

Other information

■ store between 20-25°C (68-77°F).
■ tamper evident: do not use if carton is open or if packets are torn or open.
■ see below for lot number and expiration date

Inactive Ingredients

cocoa butter, confectioners sugar, crospovidone, lactose, maltodextrin, methacrylic acid copolymer, microcrystalline cellulose, modified cornstarch, flavor, polyethylene glycol, polysorbate 80, povidone, pregelatinized starch, silicon dioxide, sodium lauryl sulfate, sorbitan monostearate, starch, sucralose, sugar, talc, triethyl citrate

Principal Display Panel

Capricorn Pharma
ORIGINAL DEVELOPERS AND MANUFACTURERS
Compare to the active ingredients of Mucinex Cough Mini-Melts
FOR KIDS
For ages 4-12
Expectorant plus Cough Relief
DEXTROMETHORPHAN HBr 5mg - Cough Suppressant
GUAIFENESIN 100mg - Expectorant
Relieves Chest Congestion
Thins and loosens mucus
Controls cough
Great taste, Easy to Take
FLASHBEADS
12 Packets
Orange Flavor